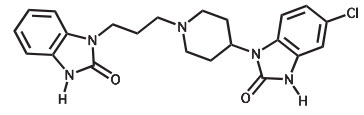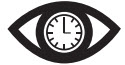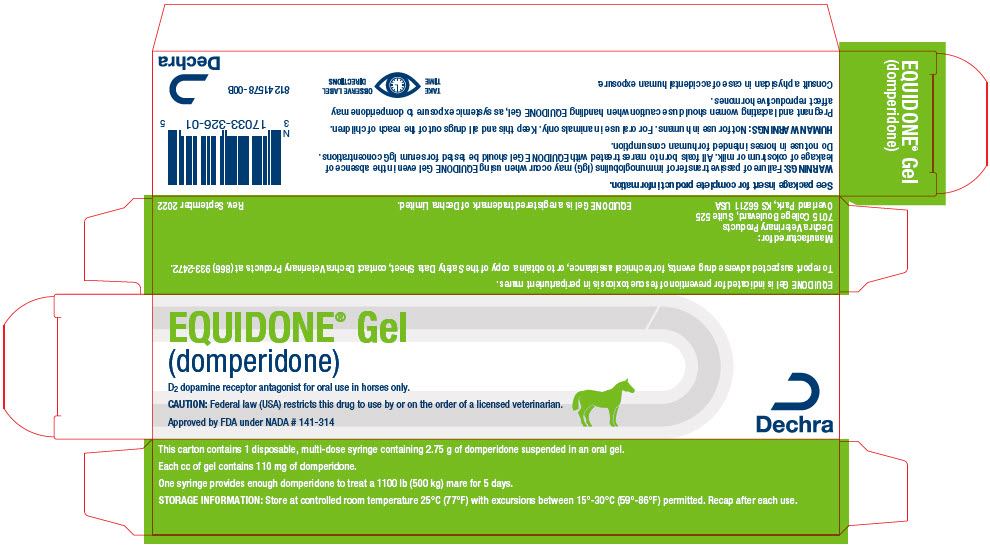 DRUG LABEL: Equidone
NDC: 17033-326 | Form: GEL
Manufacturer: Dechra Veterinary Products
Category: animal | Type: PRESCRIPTION ANIMAL DRUG LABEL
Date: 20231212

ACTIVE INGREDIENTS: domperidone 110 mg/1 mL

EQUIDONE® Gel
(domperidone)

For oral use in horses only.

CAUTION

Federal law (USA) restricts this drug to use by or on the order of a licensed veterinarian.

DESCRIPTION

Domperidone is a D2 dopamine receptor antagonist. Chemically, domperidone is 6-chloro-3-[1-[3-(2-oxo-3H-benzimidazol-1-yl)propyl]piperidin-4-yl]-1H-benzimidazol-2-one. The structural formula is:

Molecular Formula: C22H24CIN5O2 Molecular Weight: 425.91

INDICATION

For prevention of fescue toxicosis in periparturient mares.

DOSAGE AND ADMINISTRATION

Orally administer 0.5 mg/lb (1.1 mg/kg) once daily starting 10 to 15 days prior to Expected Foaling Date (EFD). Treatment may be continued for up to 5 days after foaling if mares are not producing adequate milk after foaling.

DIRECTIONS FOR ADMINISTRATION

1. Determine the appropriate dose for the body weight of the mare based on the dosing table below. One cc will treat 220 lb (100 kg) of body weight.
  Table 1. Dosing Table
  Weight (lb) | Weight (kg) | cc | Domperidone (mg)
  550-660 | 250-300 | 3 | 330
  661-880 | 301-400 | 4 | 440
  881-1100 | 401-500 | 5 | 550
  1101-1320 | 501-600 | 6 | 660
2. Turn the dial ring until the edge of the ring nearest the tip of the syringe lines up with the dose to be delivered.
3. Remove the syringe cap.
4. Make sure the horse's mouth is free of food or other obstructions.
5. Insert the nozzle of the syringe through the interdental space of the horse's mouth and deposit the gel on the back of the tongue by depressing the plunger.
6. Recap the syringe.

This is a 25 cc multi-dose syringe. Please note that for subsequent doses, it will be necessary to adjust for previous doses. For example, if the intended dose for a horse is 5 cc, then the dial ring is set at 5 cc for the first dose, at 10 cc for the second dose, at 15 cc for the third dose, at 20 cc for the fourth dose, and at 25 cc for the fifth dose.

CONTRAINDICATIONS

Horses with hypersensitivity to domperidone should not receive EQUIDONE Gel.

WARNINGS

Failure of passive transfer of immunoglobulins (IgG) may occur when using EQUIDONE Gel even in the absence of leakage of colostrum or milk. All foals born to mares treated with EQUIDONE Gel should be tested for serum IgG concentrations. Do not use in horses intended for human consumption.

HUMAN WARNINGS

Not for use in humans. For oral use in animals only. Keep this and all drugs out of the reach of children. Pregnant and lactating women should use caution when handling EQUIDONE Gel, as systemic exposure to domperidone may affect reproductive hormones. Domperidone is not approved for any indication in humans in the US. The safety of domperidone in lactating women and their nursing children has not been evaluated. Consult a physician in case of accidental human exposure.

PRECAUTIONS

EQUIDONE Gel may lead to premature birth, low birth weight foals or foal morbidity if administered >15 days prior to the expected foaling date. Accurate breeding date(s) and an expected foaling date are needed for the safe use of EQUIDONE Gel. The safety of EQUIDONE Gel has not been evaluated in breeding, pregnant and lactating mares other than in the last 45 days of pregnancy and the first 15 days of lactation (see Animal Safety). The safety in stallions has not been evaluated. The long term effects on foals born to mares treated with EQUIDONE Gel have not been evaluated.

Do not use in horses with suspected or confirmed gastrointestinal blockage, as domperidone is a prokinetic drug (it stimulates gut motility).

Use of EQUIDONE Gel may cause a false positive on the milk calcium test used to predict foaling.

Domperidone is a known P-glycoprotein substrate1 and its main metabolic pathway in humans is through CYP3A4. Significant inhibition of domperidone metabolism may occur when co-administered with drugs such as erythromycin^2 and ketoconazole^3. This could result in significantly greater domperidone drug exposure (multi-fold increase) when used with these drugs.

ADVERSE REACTIONS

The most common adverse reactions associated with treatment with EQUIDONE Gel are premature lactation (dripping of milk prior to foaling) and failure of passive transfer.

In a laboratory effectiveness study with 32 periparturient mares (17 treated with EQUIDONE Gel and 15 treated with vehicle control) 3/17 (18%) mares treated with EQUIDONE Gel experienced premature lactation. In the 25 foals (16 foals of mares treated with EQUIDONE Gel and 9 foals of vehicle control mares) evaluated for passive transfer, failure of passive transfer occurred in 13/16 (81%) foals of mares treated with EQUIDONE Gel and 8/9 (89%) foals of control mares. Failure of passive transfer in foals of mares treated with EQUIDONE Gel was not solely due to physical loss of colostrum through premature lactation, because 77% of EQUIDONE Gel treated mares that did not drip milk prior to foaling had foals with failure of passive transfer.

In a field study with 279 periparturient mares treated with EQUIDONE Gel, premature lactation was reported in 3 mares (1%) and failure of passive transfer was reported in 3 foals (1%).

In two additional field studies, a total of 2,556 mares were treated with EQUIDONE Gel or a bioequivalent formulation for 2,730 breeding seasons. Horses in these studies were treated with EQUIDONE Gel for varying durations. Of the 2,730 breeding seasons evaluated, premature lactation was reported in 262 mares (9.6%), failure of passive transfer was reported in 50 foals (1.8%), and premature parturition (gestation length ≤320 days) occurred in 13 mares (<0.5%).

To report suspected adverse events, for technical assistance or to obtain a copy of the Safety Data Sheet (SDS), contact Dechra at (866) 933-2472.

For additional information about adverse drug experience reporting for animal drugs, contact FDA at 1-888-FDA-VETS, or online at http://www.fda.gov/reportanimalae

INFORMATION FOR HORSE OWNERS

Owners should be aware that treatment with EQUIDONE Gel may result in failure of passive transfer of immunoglobulins to the foal and that this may occur even when the mare does not drip milk. Owners should be advised that all foals born to mares treated with EQUIDONE Gel should be tested for serum immunoglobulin (IgG) concentrations. Owners should be informed that EQUIDONE Gel causes false positives on the milk calcium test used to predict foaling. Owners should be directed on the proper use of the multi-dose dosing syringe, including how to set the dial ring for accurate dosing after the first dose.

CLINICAL PHARMACOLOGY

Domperidone is a D2 dopamine receptor antagonist that blocks the agonistic action of fescue alkaloids at the cellular level. Unlike other D2 antagonist drugs, domperidone does not readily cross the blood-brain barrier^4. Distribution studies with radio-labeled drug in animals have shown wide tissue distribution, but low brain concentration. Small amounts of the drug cross the placenta in rats^5. In humans, domperidone is 91-93% bound to plasma proteins. Domperidone in humans undergoes rapid and extensive hepatic metabolism by hydroxylation and N-dealkylation^1. Urinary and fecal excretions of domperidone in humans amount to 31 and 66% of the oral dose, respectively. The proportion of the drug excreted unchanged in humans is small (10% of fecal excretion and approximately 1% of urinary excretion). The average terminal plasma half-life of domperidone administered orally to horses is approximately 6 hours with very low systemic bioavailability.

EFFECTIVENESS

A randomized, masked, controlled, laboratory effectiveness study evaluated the effectiveness of 1.1 mg/kg EQUIDONE Gel administered once daily beginning 10 to 15 days prior to the expected foaling date (EFD - defined as 340 days after the median breeding) and continuing up to 5 days after foaling for the prevention of fescue toxicosis. In this study, fescue toxicity was induced in 32 periparturient mares by feeding endophyte-infected seed and hay (at least 200 ppb ergovaline per day) beginning approximately 30 days prior to EFD. A total of 17 mares were treated with EQUIDONE Gel and 15 mares were treated with a vehicle control. Twenty-seven mares (13 EQUIDONE Gel and 14 vehicle control) were included in the statistical analysis. Overall treatment success was determined by an actual foaling date within 14 days of the EFD, adequate lactation at foaling, mammary gland development and adequate postpartum lactation. EQUIDONE Gel was superior to the vehicle control.

Table 2. Treatment Success
Treatment Group (number mares) | Treatment Success | Pearson X^2 Test
Vehicle Control (14) | 7% (1 / 14) | Test statistic = 16.320
EQUIDONE Gel (13) | 92% (12 / 13) | p-value < 0.0000

Table 3. Gestation Length, Milk Production and Mammary Gland Development
Treatment Group (number mares) | Mean gestation length in days | Percent adequate milk production at foaling | Percent adequate mammary gland development at foaling
Vehicle Control (14) | 346 | 33% (3 / 9) [Three mares rescued prior to foaling for exceeding EFD by ≥15 days, 1 euthanized after foaling, 1 missing observation] | 30% (3 / 10) [Three mares rescued prior to foaling for exceeding EFD by ≥15 days, 1 euthanized after foaling]
EQUIDONE Gel (13) | 337 | 100% (13 / 13) | 100% (13 / 13)
Test Statistic | t statistic = 3.754 p = 0.0014 | Pearson X^2 = 8.793 p = 0.0030 | Pearson X^2 = 9.984 p = 0.0016

One mare treated with EQUIDONE Gel was carrying twins. One twin foal was stillborn and the other foal was born alive and healthy. Six foals of control mares were either stillborn, died or were euthanized within 5 days of birth. Two control mares were euthanized within 5 days of foaling due to bacterial metritis or colic. Dystocia occurred in 1 mare treated with EQUIDONE Gel and 4 control mares. One mare treated with EQUIDONE Gel and three control mares experienced retained placentas.

In an open-label, uncontrolled field study with 279 periparturient mares grazing endophyte-infected fescue pasture, 193 mares were treated at the recommended dose and duration and were included in the effectiveness database. Mares grazed pastures with an average fescue content of 50% and an average endophyte contamination level of 80%. The mares had an average gestation length of 340 days. Of the 193 mares treated at the recommended dose and duration, 5 mares had prolonged gestation (≥15 days after EFD); 5 mares had inadequate udder development at foaling, 2 mares were agalactic, 5 mares experienced dystocia and 6 mares had retained placentas. Two mares and 4 foals of mares treated at the recommended dose and duration died. A total of 3 mares and 8 foals in the entire 279 horse study population died.

ANIMAL SAFETY

In a target animal safety study EQUIDONE Gel was administered orally to 32 healthy periparturient mares once daily at 0X, 1X, 3X or 5X the maximum exposure dose estimated for a 550 lb mare. Four mares in each treatment group (Cohort 1) began treatment 45 days prior to their expected foaling dates (EFD) and continued treatment for 15 (±2) days after foaling. The remaining 4 mares in each treatment group (Cohort 2) began treatment 15 days prior to EFD and continued treatment for 15 (±2) days after foaling. Mares in the 0X and 3X groups were rebred and the mares and their foals were followed to 50 days of gestation. EFD was calculated as 340 days after the median breeding date.

Table 4. Treatment Groups
 |  | Number of mares started on treatment:
Treatment group | Dose | 45 days before EFD (Cohort 1) | 15 days before EFD (Cohort 2)
1 | (0X) 0.0 mg/kg [Control mares were administered vehicle at a volume equivalent to the 3X group] | 4 | 4
2 | (1X) 1.46 mg/kg | 4 | 4
3 | (3X) 4.38 mg/kg | 4 | 4
4 | (5X) 7.30 mg/kg | 4 | 4

Mares treated with EQUIDONE Gel had a higher incidence of premature parturition. There was a significant decrease in gestation length, with corresponding lower birth weights of foals, in mares treated with EQUIDONE Gel beginning 45 days prior to EFD (Cohort 1). Mares treated with EQUIDONE Gel beginning 45 days prior to EFD foaled an average of 27 days early (range 12 to 40 days early). Mares treated with EQUIDONE Gel beginning 15 days prior to EFD foaled an average of 5 days early (range 12 days early to 5 days late). (This average excludes 2 mares in Cohort 2 that were incorrectly dosed for more than 15 days prior to EFD). Control mares (both cohorts combined) foaled an average of 2 days early (range 30 days early to 10 days late).

Premature parturition resulted in low foal birth weights and may have contributed to morbidity and mortality in foals (both treated and control) in Cohort 1. Four out of 12 foals born to mares treated with EQUIDONE Gel in Cohort 1 died or were euthanized within 11 days of birth. These foals were born 12 to 40 days early. One control foal in Cohort 2 (born 30 days early) died at 14 days. Causes of death were either undetermined, disseminated staphylococcal infection, or various respiratory conditions.

Mares treated with EQUIDONE Gel had a higher incidence of dripping milk (96%) prior to parturition than control mares (50%). More mares treated with EQUIDONE Gel (71%) dripped milk for 3 or more days prior to parturition than control mares (0%).

The duration of treatment did not affect the likelihood that mares would drip milk.

Table 5. Number of Mares Dripping Milk for 3 or More Days Prior to Foaling
Cohort | 0X | 1X | 3X | 5X
1 | 0 | 3 | 3 | 4
2 | 0 | 2 | 2 | 4

Failure of passive transfer occurred in all groups; however, there was a greater incidence of IgG concentrations <400 mg/dL in foals of mares treated with EQUIDONE Gel. The incidence of failure of passive transfer also increased with dose. All mares that dripped milk for 3 or more days prior to parturition had foals with IgG concentrations <800 mg/dL, and one treated mare that did not drip milk had a foal with an IgG concentration of 400-800 mg/dL.

Table 6. Serum IgG Concentrations of Foals
 |  | # Foals (percentage) |  |  | Overall incidence of <800 mg/dL
Treatment group | # Foals | <400 mg/dL | 400-800 mg/dL | ≥800 mg/dL | Overall incidence of <800 mg/dL
0X | 8 | 3 (38%) | 2 (25%) | 3 (38%) | 63%
1X | 6 [IgG concentrations were not determined for 3 foals] | 3 (50%) | 1 (17%) | 2 (33%) | 67%
3X | 7 | 5 (71%) | 1 (14%) | 1 (14%) | 86%
5X | 8 | 7 (88%) | 1 (13%) | 0 (0%) | 100%

Foals of mares treated with EQUIDONE Gel experienced more diarrhea and loose stool than foals of control mares during the treatment phase (first 15 days of life). All episodes of diarrhea were self-limiting and resolved without treatment.

Table 7. Foals Experiencing at Least One Episode of Diarrhea or Loose Stool
Treatment group (n=8 foals/group) | # Foals (percentage)
0X | 1 (12.5%)
1X | 4 (50%)
3X | 6 (75%)
5X | 5 (63%)

Mares treated with EQUIDONE Gel generally had higher white blood cell counts (WBC) and/or granulocyte counts and gamma glutamyl transferase (GGT) and/or alkaline phosphatase (ALP) concentrations than control mares. GGT and ALP elevations occurred mostly at time points surrounding foaling, and demonstrated a declining trend post-foaling; however, the concentrations had not returned to normal in all mares by Day 15 post-foaling. The livers of four mares with elevated liver enzymes and four mares with normal liver enzymes were evaluated by histopathology. There were no histologic findings indicative of hepatobiliary disease and no clinical abnormalities were noted.

More foals of mares treated with EQUIDONE Gel had granulocyte and/or neutrophil counts below the reference range on the day of foaling than foals born to control mares. The decreased neutrophil counts in foals of mares treated with EQUIDONE Gel occurred more commonly in foals born more than 25 days prior to EFD. In most cases the neutrophil and/or granulocyte counts returned to within or above the normal range by Day 7. Foals of mares treated with EQUIDONE Gel had higher ALP concentrations than foals of control mares. Additionally, several foals of mares treated with EQUIDONE Gel also had elevations in GGT

All mares that were examined ultrasonographically exhibited foal heat (follicle ≥35 mm) within 1 to 2 weeks after foaling with the exception of a 5X mare which exhibited foal heat 23 days after foaling. Of the 12 mares that were rebred in the 0X and 3X groups, 8 (4 in the 3X group and 4 controls) were reproductive successes, and 4 (1 in the 3X group and 3 controls) were reproductive failures.

Table 8. Rebreeding Success Rates
Treatment group | # Mares bred | Pregnant at Day 50 (percentage)
0X | 7 | 4 (57%)
3X | 5 | 4 (80%)

STORAGE INFORMATION

Store at controlled room temperature 25°C (77°F) with excursions between 15°-30°C (59°-86°F) permitted. Recap after each use.

HOW SUPPLIED

EQUIDONE Gel is supplied in disposable, multi-dose, 25 cc syringes, each containing 2.75 g of domperidone suspended in an oral gel. Each cc of gel contains 110 mg of domperidone. The net weight of each syringe is approximately 26 g. Syringe is supplied in a single carton.

Approved by FDA under NADA # 141-314

REFERENCES

^1Pal D and Mitra AK. MDR- and CYP3A4-Mediated Drug-Drug Interactions. Journal of Neuroimmune Pharmacology 1: 323-339; 2006.

^2Ung D, Parkman HP, and Nagar S. Metabolic Interactions Between Prokinetic Agents Domperidone and Erythromycin: an in vitro Analysis. Xenobiotica 39(10): 749-756; 2009.

^3Medicines Control Council. Interaction Between Ketoconazole and Domperidone and the Risk of QT Prolongation-Important Safety Information. South African Medical Journal 96(7): 596; 2006.

^4The European Agency for the Evaluation of Medicinal Products. Motilium and Associated Names (London, 2002).

^5Heykants J, Knaeps A, Meuldermans W, and Michiels M. On the Pharmacokinetics of Domperidone in Animals and Man. I. Plasma Levels of Domperidone in Rats and Dogs. Age Related Absorption and Passage through the Blood Brain Barrier in Rats. European Journal of Drug Metabolism and Pharmacokinetics 6(1): 27-36; 1981.

TAKE
TIME

OBSERVE LABEL
DIRECTIONS

Manufactured for:
Dechra Veterinary Products, 7015 College Boulevard, Suite 525, Overland Park, KS 66211 USA

EQUIDONE Gel is a registered trademark of Dechra Limited.

Rev. September 2022
81241609-03

PRINCIPAL DISPLAY PANEL - 25 mL Syringe Carton

EQUIDONE® Gel
(domperidone)

D2 dopamine receptor antagonist for oral use in horses only.

CAUTION: Federal law (USA) restricts this drug to use by or on the order of a licensed veterinarian.

Approved by FDA under NADA # 141-314

Dechra